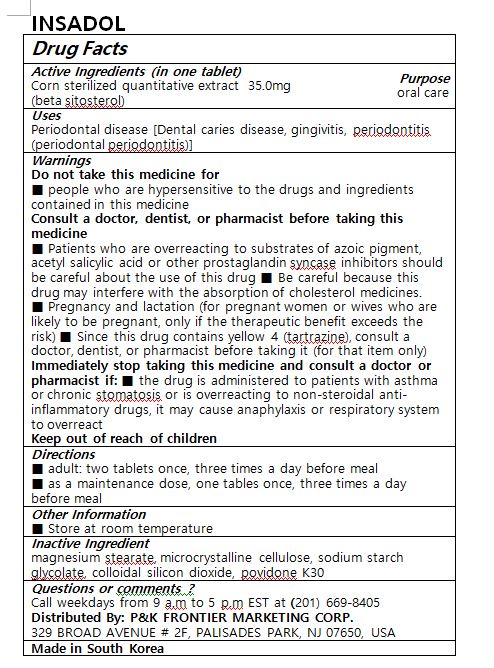 DRUG LABEL: INSADOL
NDC: 72988-0016 | Form: TABLET
Manufacturer: LYDIA Co., Ltd
Category: otc | Type: HUMAN OTC DRUG LABEL
Date: 20191007

ACTIVE INGREDIENTS: .BETA.-SITOSTEROL 35 mg/1 1
INACTIVE INGREDIENTS: POVIDONE K30; SODIUM STARCH GLYCOLATE TYPE A CORN; POWDERED CELLULOSE; MAGNESIUM STEARATE

ACTIVE INGREDIENT

Corn sterilized quantitative extract (beta sitosterol)

PURPOSE

Periodontal disease [Dental caries disease, gingivitis, periodontitis (periodontal periodontitis)]

Keep out of reach of children

INDICATIONS AND USAGE

■ adult: two tablets once, three times a day before meal

■ as a maintenance dose, one tablet once, three times a day before meal

WARNINGS

Do not take this medicine if

■ people who are hypersensitive to the drugs and ingredients contained in this medicine

Consult a doctor, dentist, or pharmacist before taking this medicine

■ Patients who are overreacting to substrates of azoic pigment, acetyl salicylic acid or other prostaglandin syncase inhibitors should be careful about the use of this drug ■ Be careful because this drug may interfere with the absorption of cholesterol medicines.

■ Pregnancy and lactation (for pregnant women or wives who are likely to be pregnant, only if the therapeutic benefit exceeds the risk) ■ Since this drug contains yellow 4 (tartrazine), consult a doctor, dentist, or pharmacist before taking it (for that item only)

Immediately stop taking this medicine and consult a doctor or pharmacist if: ■ the drug is administered to patients with asthma or chronic stomatosis or is overreacting to non-steroidal anti-inflammatory drugs, it may cause anaphylaxis or respiratory system to overreact

INACTIVE INGREDIENT

magnesium stearate, microcrystalline cellulose, sodium starch glycolate, colloidal silicon dioxide, povidone K30

DOSAGE AND ADMINISTRATION

For oral use only